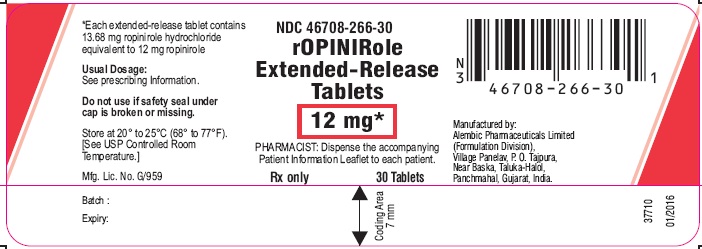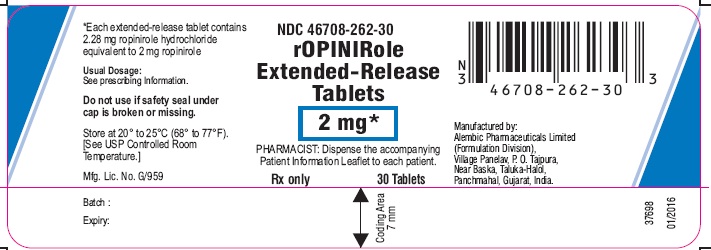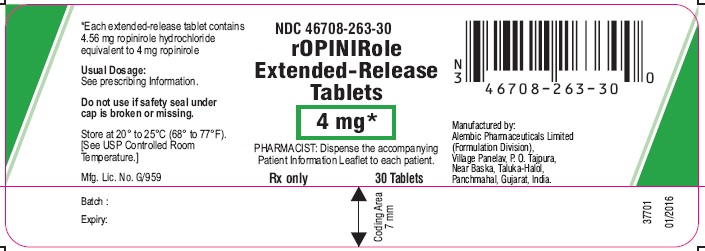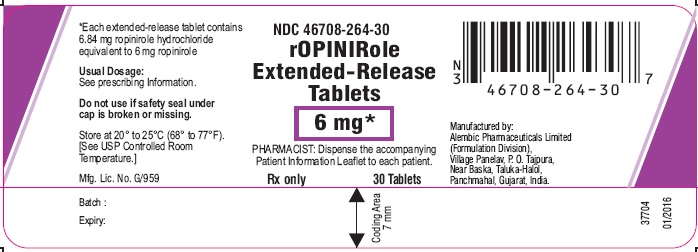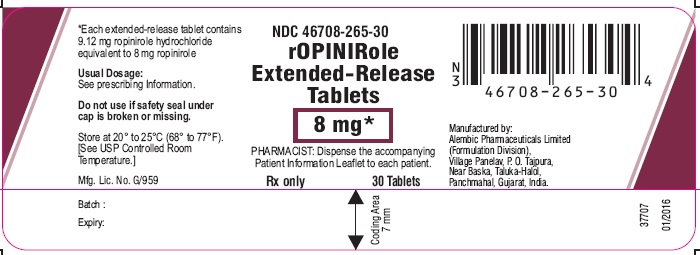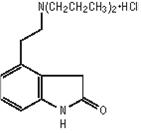 DRUG LABEL: Ropinirole
NDC: 46708-262 | Form: TABLET, FILM COATED, EXTENDED RELEASE
Manufacturer: Alembic Pharmaceuticals Limited
Category: prescription | Type: Human Prescription Drug Label
Date: 20230127

ACTIVE INGREDIENTS: ROPINIROLE HYDROCHLORIDE 2 mg/1 1
INACTIVE INGREDIENTS: HYPROMELLOSE, UNSPECIFIED; HYDROGENATED CASTOR OIL; CARBOXYMETHYLCELLULOSE SODIUM; STARCH, CORN; POVIDONE, UNSPECIFIED; SILICON DIOXIDE; MAGNESIUM STEARATE; ETHYLCELLULOSE (7 MPA.S); TITANIUM DIOXIDE; POLYETHYLENE GLYCOL 6000; TALC; FERRIC OXIDE RED

HIGHLIGHTS OF PRESCRIBING INFORMATION

These highlights do not include all the information needed to use ROPINIROLE EXTENDED-RELEASE TABLETS safely and effectively. See full prescribing information for ROPINIROLE EXTENDED-RELEASE TABLETS.
ROPINIROLE extended-release tablets, for oral use
Initial U.S. Approval: 1997

RECENT MAJOR CHANGES

Dosage and Administration (2.2, 2.3) 8/2014

Contraindications (4) 8/2014

Warnings and Precautions (5.5, 5.7) 8/2014

1 INDICATIONS AND USAGE

Ropinirole extended-release tablets are non-ergoline dopamine agonist indicated for the treatment of Parkinson’s disease (1.1)

2 DOSAGE AND ADMINISTRATION

•Ropinirole extended-release tablets are taken once daily, with or without food; tablets must be swallowed whole and must not be chewed, crushed, or divided (2.1)
•The recommended starting dose is 2 mg taken once daily for 1 to 2 weeks; the dose should be increased by 2 mg/day at 1 week or longer intervals; the maximum dose is 24 mg/day (2.2, 14.2)
•Renal Impairment: In patients with end-stage renal disease on hemodialysis, the maximum recommended dose is 18 mg/day (2.2)
•If ropinirole extended-release tablets must be discontinued, it should be tapered gradually over a 7-day period; retitration of ropinirole extended-release tablets may be warranted if therapy is interrupted (2.1, 2.2)
•Patients may be switched directly from immediate-release ropinirole to ropinirole extended-release tablets; the initial switching dose of ropinirole extended-release tablets should most closely match the total daily dose of immediate-release ropinirole. (2.3)

3 DOSAGE FORMS AND STRENGTHS

Tablets: 2 mg, 4 mg, 6 mg, 8 mg, and 12 mg (3)

4 CONTRAINDICATIONS

History of hypersensitivity/ allergic reaction (including urticaria, angioedema, rash, pruritus) to ropinirole or to any of the excipients (4)

5 WARNINGS AND PRECAUTIONS

•Sudden onset of sleep and somnolence may occur (5.1)
•Syncope may occur (5.2)
•Hypotension, including orthostatic hypotension may occur (5.3)
•Elevation of blood pressure and changes in heart rate may occur (5.4)
•May cause hallucinations and psychotic-like behaviors (5.5)
•May cause or exacerbate dyskinesia (5.6)
•May cause problems with impulse control or compulsive behaviors (5.7)

6 ADVERSE REACTIONS

· Most common adverse reactions (incidence for ropinirole extended-release tablets at least 5% greater than placebo) in advanced Parkinson’s disease with concomitant L-dopa were dyskinesia, nausea, dizziness, hallucination. (6.1)

· Most common adverse reactions (incidence incidence for ropinirole extended-release tablets at least 5%) in early Parkinson’s disease without L-dopa were nausea, somnolence, abdominal pain/discomfort, dizziness, headache, and constipation (6.1)
To report SUSPECTED ADVERSE REACTIONS, contact FDA at 1-800-FDA-1088 or www.fda.gov/medwatch

7 DRUG INTERACTIONS

•Inhibitors or inducers of CYP1A2: May alter the clearance of ropinirole;dose adjustment may be required (7.1, 12.3)
•Hormone replacement therapy (HRT): Starting or stopping HRT treatment may require dose adjustment of ropinirole extended-release tablets (7.2, 12.3)
•Dopamine antagonists (e.g., neuroleptics metoclopramide): May reduce efficacy of ropinirole extended-release tablets (7.3)

8 USE IN SPECIFIC POPULATIONS

Pregnancy: Based on animal data, may cause fetal harm (8.1)

FULL PRESCRIBING INFORMATION

1 INDICATIONS AND USAGE

1.1 Parkinson's Disease

Ropinirole extended-release tablets are indicated for the treatment of Parkinson’s disease.

2 DOSAGE AND ADMINISTRATION

2.1 General Dosing Recommendations

· Ropinirole extended-release tablets are taken once daily, with or without food [see Clinical Pharmacology (12.3)].

· Tablets must be swallowed whole and must not be chewed, crushed, or divided.

· If a significant interruption in therapy with ropinirole extended-release tablets has occurred, retitration of therapy may be warranted.

2.2 Dosing for Parkinson's Disease

The starting dose is 2 mg taken once daily for 1 to 2 weeks, followed by increases of 2 mg/day at 1-week or longer intervals as appropriate, based on therapeutic response and tolerability. The maximum recommended dose of ropinirole extended-release tablets is 24 mg/day.

In clinical trials, dosage was initiated at 2 mg/day and gradually titrated based on individual patient therapeutic response and tolerability. Doses greater than 24 mg/day have not been studied in clinical trials. Patients should be assessed for therapeutic response and tolerability at a minimal interval of 1 week or longer after each dose increment. Monitor patients during dose titration because too rapid a rate of titration may lead to dose selection that may not provide additional benefit, but that may increase the risk of adverse reactions [see Clinical Studies (14.2)]. Due to the flexible dosing design used in clinical trials, specific dose-response information could not be determined.

Ropinirole extended-release tablets should be discontinued gradually over a 7-day period.

Renal Impairment

No dose adjustment is necessary in patients with moderate renal impairment (creatinine clearance of 30 to 50 mL/min). The recommended initial dose of ropinirole extended-release tablets for patients with end-stage renal disease on hemodialysis is 2 mg once daily. Further dose escalations should be based on tolerability and need for efficacy. The recommended maximum total daily dose is 18 mg/day in patients receiving regular dialysis. Supplemental doses after dialysis are not required. The use of ropinirole extended-release tablets in patients with severe renal impairment without regular dialysis has not been studied.

2.3 Switching from Immediate-Release Ropinirole Tablets to Extended-Release Ropinirole Tablets

Patients may be switched directly from immediate-release ropinirole to extended-release ropinirole tablets. The initial dose of ropinirole extended-release tablets should most closely match the total daily dose of the immediate-release formulation of ropinirole tablets, as shown in Table 1.

Table 1. Conversion from Immediate-Release Ropinirole Tablets to Extended-Release Ropinirole Tablets

Immediate-Release Ropinirole Tablets Total Daily Dose (mg) | Extended-Release Ropinirole Tablets Total Daily Dose (mg)
0.75 to 2.25 | 2
3 to 4.5 | 4
6 | 6
7.5 to 9 | 8
12 | 12
15 | 16
18 | 18
21 | 20
24 | 24

Following conversion to ropinirole extended-release tablets, the dose may be adjusted depending on therapeutic response and tolerability [see Dosage and Administration (2.2)].

2.4 Effect of Gastrointestinal Transit Time on Medication Release

Ropinirole extended-release tablets are designed to release medication over a 24-hour period. If rapid gastrointestinal transit occurs, there may be risk of incomplete release of medication and medication residue being passed in the stool.

3 DOSAGE FORMS AND STRENGTHS

- 2 mg, pink, capsule shaped, film coated tablet, debossed with ‘L191’ on one side and plain on other side.
- 4 mg, light brown, capsule shaped, film coated tablet, debossed with ‘L193’ on one side and plain on other side.
- 6 mg, white to off white, capsule shaped, film coated tablet, debossed with ‘L321’ on one side and plain on other side.
- 8 mg, dark brown to red, capsule shaped, film coated tablet, debossed with ‘L194’ on one side and plain on other side.
- 12 mg, light green, capsule shaped, film coated tablet, debossed with ‘L195’ on one side and plain on other side.

4 CONTRAINDICATIONS

Ropinirole extended-release tablets are contraindicated in patients known to have a hypersensitivity/allergic reaction including urticaria, angioedema, rash, pruritus) to ropinirole or any of the excipients.

5 WARNINGS AND PRECAUTIONS

5.1 Falling Asleep during Activities of Daily Living and Somnolence

Patients treated with ropinirole have reported falling asleep while engaged in activities of daily living, including driving or operating machinary, which sometimes resulted in accidents. Although many of these patients reported somnolence while on ropinirole, some perceived that they had no warning signs such as excessive drowsiness, and believed that they were alert immediately prior to the event. Some have reported these events more than 1 year after initiation of treatment.

Among the 613 patients who received ropinirole extended-release tablets in clinical trials, there were 5 cases of sudden onset of sleep and 2 cases of motor vehicle accident in which it is not known if falling asleep was a contributing factor.

During the 6-month trial in advanced Parkinson’s disease, somnolence was reported in 7% of patients receiving ropinirole extended-release tablets compared with 4% of patients receiving placebo. During the 36-week trial in early Parkinson’s disease, somnolence was reported in 11% of patients receiving ropinirole extended-release tablets compared with 15% of patients receiving the immediate-release formulation of ropinirole tablets[see Adverse Reactions (6.1)]. However, because dose-response was not systematically studied with ropinirole extended-release tablets, the occurrence of somnolence at the highest recommended doses may be higher than these reported frequencies [see Adverse Reactions (6.1)].

It has been reported that falling asleep while engaged in activities of daily living usually occurs in a setting of preexisting somnolence, although patients may not give such a history. For this reason, prescribers should reassess patients for drowsiness or sleepiness, especially since some of the events occur well after the start of treatment. Prescribers should also be aware that patients may not acknowledge drowsiness or sleepiness until directly questioned about drowsiness or sleepiness during specific activities.

Before initiating treatment with ropinirole extended-release tablets, patients should be advised of the potential to develop drowsiness and specifically asked about factors that may increase the risk with ropinirole extended-release tablets such as concomitant sedating medications, the presence of sleep disorders, and concomitant medications that increase ropinirole plasma levels (e.g., ciprofloxacin) [see Drug Interactions (7.1)]. If a patient develops significant daytime sleepiness or episodes of falling asleep during activities that require active participation (e.g., driving a motor vehicle, conversations, eating), ropinirole extended-release tablets should ordinarily be discontinued [see Dosage and Administration (2.2)]. If a decision is made to continue ropinirole extended-release tablets, patients should be advised to not drive and to avoid other potentially dangerous activities. There is insufficient information to establish that dose reduction will eliminate episodes of falling asleep while engaged in activities of daily living.

5.2 Syncope

Syncope, sometimes associated with bradycardia, was observed in association with ropinirole extended-release tablets in Parkinson’s disease patients. In a placebo-controlled trial involving patients with advanced Parkinson’s disease, syncope occurred in 2 of the 202 patients (1%) who received ropinirole extended-release tablets, and in none of the 191 patients who received placebo [see Adverse Reactions (6.1)].

Because the trial of ropinirole extended-release tablets excluded patients with significant cardiovascular disease, patients with significant cardiovascular disease should be treated with caution.

5.3 Hypotension/Orthostatic Hypotension

Dopamine agonists, in clinical trials and clinical experience, appear to impair the systemic regulation of blood pressure, with resulting orthostatic hypotension, especially during dose escalation. In addition, patients with Parkinson’s disease appear to have an impaired capacity to respond to a postural challenge. For these reasons, patients should be monitored for signs and symptoms of orthostatic hypotension, especially during dose escalation, and patients should be informed of the risk for syncope and hypotension [see Patient Counseling Information (17)].

In a placebo-controlled trial involving patients with advanced Parkinson’s disease, hypotension was reported as an adverse event in 5 of 202 patients (2%) receiving ropinirole extended-release tablets and in none of the 191 patients receiving placebo. Orthostatic hypotension was reported as an adverse event in 5% of patients receiving ropinirole extended-release tablets, and in 1% of placebo recipients [see Adverse Reactions (6.1)].

An analysis of the randomized, double-blinded, placebo-controlled trial in advanced Parkinson’s disease was conducted using a variety of adverse event terms possibly suggestive of hypotension, including hypotension, orthostatic hypotension, dizziness, vertigo, and blood pressure decreased. This analysis showed a higher incidence of these events with ropinirole extended-release tablets (7%, 15 of 202) vs. placebo (3%, 6 of 191). The increased incidence with ropinirole extended-release tablets was observed in a setting in which patients were very carefully titrated, and patients with clinically relevant cardiovascular disease or symptomatic orthostatic hypotension at baseline had been excluded from this trial. Orthostatic vital signs (semi-supine to standing) were monitored throughout the advanced Parkinson’s disease trial and changes related to ropinirole extended-release tablets (compared with placebo) from baseline were assessed.

The frequency of orthostatic hypotension at any time during the trial was 38% for ropinirole extended-release tablets vs. 31% for placebo for mild to moderate systolic blood pressure decrements (≥20 mm Hg), 63% for ropinirole extended-release tablets vs. 58% for placebo for mild-to-moderate diastolic blood pressure decrements (≥10 mm Hg), 10% for ropinirole extended-release tablets vs. 7% for placebo for severe diastolic blood pressure decrements (≥20 mm Hg), and 23% for ropinirole extended-release tablets vs. 19% for placebo for mild-to-moderate combined systolic and diastolic blood pressure decrements.

Significant decrements in blood pressure unrelated to standing were also reported in some patients taking ropinirole extended-release tablets. In the semi-supine position, the frequency was 10% for ropinirole extended-release tablets vs. 8% for placebo for severe systolic blood pressure decrease (≥40 mm Hg), and was 25% for ropinirole extended-release tablets vs. 21% for placebo for severe diastolic blood pressure decrease (≥20 mm Hg).

The increased incidence for hypotension and/or orthostatic hypotension was observed in both the titration and maintenance phases and in some cases persisted into the maintenance period after developing in the titration phase.

5.4 Elevation of Blood Pressure and Changes in Heart Rate

In the placebo-controlled trial in advanced Parkinson’s disease, there were no clear effects of ropinirole extended-release tablets on average changes in blood pressure or heart rate compared with placebo.

In the semi-supine position, the frequency was 8% for ropinirole extended-release tablets vs. 5% for placebo for severe systolic blood pressure increase (≥40 mm Hg). In the standing position, the frequency was 9% for ropinirole extended-release tablets vs. 6% for placebo for severe systolic blood pressure increase ≥40 mm Hg). In the semi-supine position, the frequency was 23% for ropinirole extended-release tablets vs. 18% for placebo for moderate pulse increase (≥15 beats/ minute), and 19% for ropinirole extended-release tablets vs. 17% for placebo for moderate pulse decrease (≥15 beats/minute). In the standing position, the frequency was 2% for ropinirole extended-release tablets vs. <1% for placebo for severe pulse increase (≥30 beats/minute), and 24% for ropinirole extended-release tablets vs. 19% for placebo for moderate pulse decrease (≥15 beats/minute).

The increased incidence for various elevations of systolic and/or diastolic blood pressure and/or changes in pulse was observed in both the titration and maintenance phases as well as persisting into the maintenance period after developing in the titration phase.

Elevation of blood pressure and/or changes in heart rate in patients taking ropinirole extended-release tablets should be considered when treating patients with cardiovascular disease.

5.5 Hallucinations/Psychotic-like Behavior

In the double-blind, placebo-controlled, advanced Parkinson’s disease trial 8% (17 of 202) of patients receiving ropinirole extended-release tablets reported hallucination compared with 2% (4 of 191) patients receiving placebo [see Adverse Reactions (6.1)]. Hallucination led to discontinuation of treatment in 2% (4 of 202) of patients on ropinirole extended-release tablets and 1% (2 of 191) of patients on placebo.

The incidence of hallucination is increased in elderly patients (i.e., older than 65 years) treated with ropinirole extended-release tablets [see Use in Specific Populations (8.5)].

Postmarketing reports indicate that patients may experience new or worsening mental status and behavioral changes, which may be severe, including psychotic-like behavior during treatment with ropinirole or after starting or increasing the dose of ropinirole. Other drugs prescribed to improve the symptoms of Parkinson’s disease can have similar effects on thinking and behavior. This abnormal thinking and behavior can consist of one or more of a variety of manifestations including paranoid ideation, delusions, hallucinations, confusion, psychotic-like behavior, disorientation, aggressive behavior, agitation, and delirium.

Patients with a major psychotic disorder should ordinarily not be treated with ropinirole extended-release tablets because of the risk of exacerbating the psychosis. In addition, certain medications used to treat psychosis may exacerbate the symptoms of Parkinson’s disease and may decrease the effectiveness of ropinirole extended-release tablets [see Drug Interactions (7.3)].

5.6 Dyskinesia

Ropinirole extended-release tablets may potentiate the dopaminergic side effects of L-dopa and may cause and/or exacerbate pre-existing dyskinesia in patients treated with L-dopa for Parkinson’s disease. In the double-blind, placebo-controlled trial in patients with advanced Parkinson’s disease dyskinesia was reported as an adverse event in 13% of patients taking ropinirole extended-release tablets and 3% of patients on placebo [see Adverse Reactions (6.1)]. Decreasing the dose of a dopaminergic drug may ameliorate this side effect.

5.7 Impulse Control/Compulsive Behaviors

Case reports suggest that patients can experience intense urges to gamble, increased sexual urges, intense urges to spend money, binge or compulsive eating, and/or other intense urges, and the inability to control these urges while taking one or more of the medications, including ropinirole extended-release tablets, that increase central dopaminergic tone and that are generally used for the treatment of Parkinson’s disease. In some cases, although not all, these urges were reported to have stopped when the dose was reduced or the medication was discontinued. Because patients may not recognize these behaviors as abnormal, it is important for prescribers to specifically ask patients or their caregivers about the development of new or increased gambling urges, sexual urges, uncontrolled spending, binge or compulsive eating, or other urges while being treated with ropinirole extended-release tablets. Physicians should consider dose reduction or stopping the medication if a patient develops such urges while taking ropinirole extended-release tablets.

5.8 Withdrawal-emergent Hyperpyrexia and Confusion

A symptom complex resembling the neuroleptic malignant syndrome (characterized by elevated temperature, muscular rigidity, altered consciousness, and autonomic instability), with no other obvious etiology, has been reported in association with rapid dose reduction, withdrawal of, or changes in dopaminergic therapy. Therefore, it is recommended that the dose be tapered at the end of treatment with ropinirole extended-release tablets as a prophylactic measure [see Dosage and Administration (2.2)].

5.9 Melanoma

Epidemiological studies have shown that patients with Parkinson’s disease have a higher risk (2 to approximately 6-fold higher) of developing melanoma than the general population. Whether the increased risk observed was due to Parkinson’s disease or other factors, such as drugs used to treat Parkinson’s disease, is unclear. In the clinical development program (N = 613), one patient treated with ropinirole extended-release tablets and also levodopa/carbidopa developed melanoma.

For the reasons stated above, patients and providers are advised to monitor for melanomas frequently and on a regular basis when using ropinirole extended-release tablets. Ideally, periodic skin examinations should be performed by appropriately qualified individuals (e.g., dermatologists).

5.10 Fibrotic Complications

Cases of retroperitoneal fibrosis, pulmonary infiltrates, pleural effusion, pleural thickening, pericarditis, and cardiac valvulopathy have been reported in some patients treated with ergot-derived dopaminergic agents. While these complications may resolve when the drug is discontinued, complete resolution does not always occur.

Although these adverse reactions are believed to be related to the ergoline structure of these compounds, whether other, non-ergot-derived dopamine agonists, such as ropinirole, can cause them is unknown.

Cases of possible fibrotic complications, including pleural effusion, pleural fibrosis, interstitial lung disease, and cardiac valvulopathy have been reported in the development program and postmarketing experience for ropinirole. In the clinical development program (N = 613), 2 patients treated with ropinirole extended-release tablets had pleural effusion. While the evidence is not sufficient to establish a causal relationship between ropinirole and these fibrotic complications, a contribution of ropinirole cannot be excluded.

5.11 Retinal Pathology

Retinal degeneration was observed in albino rats in the 2-year carcinogenicity study at all doses tested (equivalent to 0.6 to 20 times the maximum recommended human dose (MRHD) of 24 mg/day on a mg/m^2 basis), but was statistically significant at the highest dose (50 mg/kg/day). Retinal degeneration was not observed in a 3-month study in pigmented rats, in a 2-year carcinogenicity study in albino mice, or in 1-year studies in monkeys or albino rats. The significance of this effect for humans has not been established, but involves disruption of a mechanism that is universally present in vertebrates (e.g., disk shedding).

Ocular electroretinogram (ERG) assessments were conducted during a 2-year, double-blind, multicenter, flexible-dose, L-dopa-controlled clinical trial of immediate-release ropinirole in patients with Parkinson’s disease; 156 patients (78 on immediate-release ropinirole, mean dose: 11.9 mg/day and 78 on L-dopa, mean dose: 555.2 mg/day) were evaluated for evidence of retinal dysfunction through electroretinograms. There was no clinically meaningful difference between the treatment groups in retinal function over the duration of the trial.

5.12 Binding to Melanin

Ropinirole binds to melanin-containing tissues (i.e., eyes, skin) in pigmented rats. After a single dose, long-term retention of drug was demonstrated, with a half-life in the eye of 20 days.

6 ADVERSE REACTIONS

The following adverse reactions are described in more detail in other sections of the label:

· Hypersensitivity [see Contraindications (4)]

· Falling Asleep during Activities of Daily Living and Somnolence [see Warnings and Precautions (5.1)]

· Syncope [see Warnings and Precautions (5.2)]

· Hypotension/Orthostatic Hypotension [see Warnings and Precautions (5.3)]

· Elevation of Blood Pressure and Changes in Heart Rate [see Warnings and Precautions (5.4)]

· Hallucinations/Psychotic-like Behavior [see Warnings and Precautions (5.5)]

· Dyskinesia [see Warnings and Precautions (5.6)]

· Impulse Control/Compulsive Behaviors [see Warnings and Precautions (5.7)]

· Withdrawal-emergent Hyperpyrexia and Confusion [see Warnings and Precautions (5.8)]

· Melanoma [see Warnings and Precautions (5.9)]

· Fibrotic Complications [see Warnings and Precautions (5.10)]

6.1 Clinical Trials Experience

Because clinical trials are conducted under widely varying conditions, adverse reaction rates observed in the clinical trials of a drug cannot be directly compared with rates in the clinical trials of another drug (or of another development program of a different formulation of the same drug) and may not reflect the rates observed in practice.

During the premarketing development of ropinirole extended-release tablets, patients with advanced Parkinson’s disease received ropinirole extended-release tablets or placebo as adjunctive therapy in 1 clinical trial. In a second trial, patients with early Parkinson’s disease were treated with ropinirole extended-release tablets or the immediate-release formulation of ropinirole tablets without L-dopa.

Advanced Parkinson’s Disease (with L-dopa)

In the 24-week, double-blind, placebo-controlled trial for the treatment of advanced Parkinson’s disease, the most commonly observed adverse reactions in patients treated with ropinirole extended-release tablets (incidence at least 5% greater than placebo) were dyskinesia, nausea, dizziness and hallucination.

Approximately 6% of patients treated with ropinirole extended-release tablets discontinued treatment due to adverse reactions compared with 5% of patients who received placebo. The most common adverse reaction in patients treated with ropinirole extended-release tablets causing discontinuation of treatment with ropinirole extended-release tablets was hallucination (2%)

Table 2 lists treatment-emergent adverse reactions that occurred in at least 2% (and were numerically greater than placebo) of patients with advanced Parkinson’s disease treated with ropinirole extended-release tablets who participated in the 26-week, double-blind, placebo-controlled trial. In this trial, either ropinirole extended-release tablets or placebo was used as an adjunct to L-dopa.

Table 2. Treatment-Emergent Adverse Reaction Incidence in a Double-Blind, Placebo-Controlled Trial in Advanced Stage Parkinson’s Disease (With L-dopa) (Events ≥2% of Patients Treated with Ropinirole Extended-Release Tabletsand >% with Placebo)a

Body System/Adverse Reaction | Ropinirole Extended-Release Tablets (n = 202) % | Placebo (n = 191) %
Ear and labyrinth disorders
Vertigo | 4 | 2
Gastrointestinal disorders
Nausea | 11 | 4
Constipation | 4 | 2
Abdominal pain/discomfort | 6 | 3
Diarrhea | 3 | 2
Dry mouth | 2 | <1
General disorders
Edema peripheral | 4 | 1
Injury, poisoning, and procedural complication
Fall* | 2 | 1
Musculoskeletal and connective tissue disorders
Back pain | 3 | 2
Nervous system disorders
Dyskinesiab | 13 | 3
Dizziness | 8 | 3
Somnolence | 7 | 4
Psychiatric disorders
Hallucination | 8 | 2
Anxiety | 2 | 1
Vascular disorders
Orthostatic hypotension | 5 | 1
Hypotension | 2 | 0
Hypertensionb | 3 | 2

aPatients may have reported multiple adverse reactions during the trial or at discontinuation; thus, patients may be included in more than one category.

bDose-related.

Although this trial was not designed for optimally characterizing dose-related adverse reactions, there was a suggestion (based upon comparison of incidence of adverse reactions across dose ranges for ropinirole extended-release tablets and placebo) that the incidence for dyskinesia, hypertension, and fall was dose-related to ropinirole extended-release tablets.
The incidence for many adverse reactions with ropinirole extended-release tablets treatment was increased relative to placebo (i.e., the incidence in the group receiving ropinirole extended-release tablets was 2% or greater than placebo in either the titration or maintenance phases of the trial. During the titration phase, an increased incidence (shown in descending order of % treatment difference) was observed for dyskinesia, nausea, abdominal pain/discomfort, orthostatic hypotension, dizziness, vertigo, hypertension, peripheral edema, and dry mouth. During the maintenance phase, an increased incidence was observed for dyskinesia, nausea, dizziness, hallucination, somnolence, fall, hypertension, abnormal dreams, constipation, chest pain, bronchitis, and nasopharyngitis. Some adverse reactions developing in the titration phase persisted

(³7 days) into the maintenance phase. These “persistent” adverse reactions included dyskinesia, hallucination, orthostatic hypotension, and dry mouth.

The incidence of adverse reactions was not clearly different between women and men.

Early Parkinson’s Disease (without L-dopa)

In the 36–week early Parkinson’s disease trial the most commonly observed adverse reactions in patients treated with ropinirole extended-release tablets (≥5%) were nausea (19%), somnolence (11%), abdominal pain/discomfort (7%), dizziness (6%), headache (6%), and constipation (5%). The type of adverse reactions and the frequency (i.e. incidence) with which they occurred were generally similar over the whole treatment period in this trial of early Parkinson’s disease patients who were initially treated with ropinirole extended-release tablets or the immediate-release formulation of ropinirole tablets and subsequently crossed over to treatment with the other formulation.

During the titration phase, an increased incidence with ropinirole extended-release tablets compared with the immediate-release formulation of ropinirole tablets (i.e., the incidence in ropinirole extended-release tablets was 2% or greater than immediate-release ropinirole tablets), shown in descending order of % treatment difference, was observed for: constipation, hallucination, vertigo, abdominal pain/discomfort, nausea, vomiting, fall, headache, diarrhea, pyrexia, and flatulence. During the maintenance phase, an increased incidence was observed for fall, myalgia, and sleep disorder. Several adverse reactions developing in the titration phase persisted (³7 days) into the maintenance phase. These “persistent” adverse reactions included: constipation, hallucination, muscle spasms, flatulence, insomnia, sleep disorder, abdominal pain/discomfort, cough, and nasopharyngitis.

6.2 Adverse Reactions Observed during the Clinical Development of the Immediate-release Formulation of Ropinirole Tablets for Parkinson's Disease (Advanced and Early)

Because clinical trials are conducted under widely varying conditions, adverse reaction rates observed in the clinical trials of a drug cannot be directly compared with rates in the clinical trials of another drug (or of another development program of a different formulation of the same drug) and may not reflect the rates observed in practice.

In patients with advanced Parkinson’s disease who were treated with the immediate-release formulation of ropinirole tablets, the most common adverse reactions (³5% treatment difference from placebo; presented in order of decreasing treatment difference frequency) were dyskinesia (21%), somnolence (12%), nausea (12%), dizziness (10%), confusion (7%), hallucinations (6%), headache (5%), and increased sweating (5%). In patients with early Parkinson’s disease who were treated with the immediate-release formulation of ropinirole tablets, the most common adverse reactions (³5% treatment difference from placebo; presented in order of decreasing treatment difference frequency) were nausea (38%), somnolence (34%), dizziness (18%), syncope (11%), asthenic condition (11%), viral infection (8%), leg edema (6%), vomiting (5%), and dyspepsia (5%).

7 DRUG INTERACTIONS

7.1 CYP1A2 Inhibitors and Inducers

In vitro metabolism studies showed that CYP1A2 is the major enzyme responsible for the metabolism of ropinirole. There is thus the potential for inducers or inhibitors of this enzyme to alter the clearance of ropinirole. Therefore, if therapy with a drug known to be a potent inducer or inhibitor of CYP1A2 is stopped or started during treatment with ropinirole extended-release tablets, adjustment of the dose of ropinirole extended-release tablets may be required. Coadministration of ciprofloxacin, an inhibitor of CYP1A2, with immediate-release ropinirole increases the AUC and Cmax of ropinirole [see Clinical Pharmacology (12.3)]. Cigarette smoking is expected to increase the clearance of ropinirole since CYP1A2 is known to be induced by smoking [see Clinical Pharmacology (12.3)].

7.2 Estrogens

Population pharmacokinetic analysis revealed that higher doses of estrogens (usually associated with hormone replacement therapy [HRT]) reduced the clearance of ropinirole. Starting or stopping HRT may require adjustment of dosage of ropinirole extended-release tablets [see Clinical Pharmacology (12.3)].

7.3 Dopamine Antagonists

Because ropinirole is a dopamine agonist, it is possible that dopamine antagonists such as neuroleptics (e.g., phenothiazines, butyrophenones, thioxanthenes) or metoclopramide may reduce the efficacy of ropinirole extended-release tablets.

8 USE IN SPECIFIC POPULATIONS

8.1 Pregnancy

Pregnancy Category C. There are no adequate and well-controlled studies in pregnant women. In animal reproduction studies, ropinirole has been shown to have adverse effects on embryo-fetal development, including teratogenic effects. Ropinirole extended-release tablets should be used during pregnancy only if the potential benefit outweighs the potential risk to the fetus.

Oral treatment of pregnant rats with ropinirole during organogenesis resulted in decreased fetal body weight, increased fetal death, and digital malformations at 24, 36, and 60 times, respectively, the maximum recommended human dose (MRHD) for Parkinson’s disease (24 mg/day) on a mg/m^2 basis. The combined oral administration of ropinirole at 8 times the MRHD and a clinically relevant dose of L-dopa to pregnant rabbits during organogenesis produced a greater incidence and severity of fetal malformations (primarily digit defects) than were seen in the offspring of rabbits treated with L-dopa alone. No effect on fetal development was observed in rabbits when ropinirole was administered alone at an oral dose 16 times the MRHD on a mg/m^2 basis. In a perinatal-postnatal study in rats, impaired growth and development of nursing offspring and altered neurological development of female offspring were observed when dams were treated with 4 times the MRHD on a mg/m^2 basis.

8.3 Nursing Mothers

Ropinirole inhibits prolactin secretion in humans and could potentially inhibit lactation. Ropinirole has been detected in rat milk. It is not known whether this drug is excreted in human milk. Because many drugs are excreted in human milk, caution should be exercised when ropinirole is administered to a nursing woman.

8.4 Pediatric Use

Safety and effectiveness in the pediatric population have not been established.

8.5 Geriatric Use

Dose adjustment is not necessary in elderly (65 years and older) patients, as the dose of ropinirole extended-release tablets is individually titrated to clinical therapeutic response and tolerability. Pharmacokinetic trials conducted in patients demonstrated that oral clearance of ropinirole is reduced by 15% in patients above 65 years compared with younger patients [see Clinical Pharmacology (12.3)].

In clinical trials of ropinirole extended-release tablets for Parkinson’s disease, 387 patients were 65 years and older and 107 were 75 and older. Among patients receiving ropinirole extended-release tablets, hallucination was more common in elderly patients (10%) compared with non-elderly patients (2%). The incidence of overall adverse reactions increased with increasing age for both patients receiving ropinirole extended-release tablets and placebo.

8.6 Renal Impairment

No dose adjustment is necessary in patients with moderate renal impairment (creatinine clearance of 30 to 50 mL/min). For patients with end-stage renal disease on hemodialysis, a reduced maximum dose is recommended [see Dosage and Administration (2.2), Clinical Pharmacology (12.3)]. The use of ropinirole extended-release tablets in patients with severe renal impairment (creatinine clearance less than 30 mL/min) without regular dialysis has not been studied.

8.7 Hepatic Impairment

The pharmacokinetics of ropinirole have not been studied in patients with hepatic impairment.

10 OVERDOSAGE

The symptoms of overdose with ropinirole are generally related to its dopaminergic activity. General supportive measures are recommended. Vital signs should be maintained, if necessary. In the Parkinson’s disease program, there have been patients who accidentally or intentionally took more than their prescribed dose of ropinirole. The largest overdose reported with immediate-release ropinirole in clinical trials was 435 mg taken over a 7-day period (62.1 mg/day). Of patients who received a dose greater than 24 mg/day, reported symptoms included adverse events commonly reported during dopaminergic therapy (nausea, dizziness), as well as visual hallucinations, hyperhidrosis, claustrophobia, chorea, palpitations, asthenia, and nightmares. Additional symptoms reported for doses of 24 mg or less or for overdoses of unknown amount included vomiting, increased coughing, fatigue, syncope, vasovagal syncope, dyskinesia, agitation, chest pain, orthostatic hypotension, somnolence, and confusional state.

11 DESCRIPTION

Ropinirole extended-release tablets contains ropinirole, a non-ergoline dopamine agonist as the hydrochloride salt. The chemical name of ropinirole hydrochloride is 4-[2-(dipropylamino)ethyl]-1,3-dihydro-2H-indol-2-one and the empirical formula is C16H24N2O•HCl. The molecular weight is 296.84 (260.38 as the free base).

The structural formula is:

Ropinirole hydrochloride is a white to yellow solid with a melting range of 243° to 250°C and a solubility of 133 mg/mL in water.
Each capsule shaped, film coated tablet contains 2.28 mg, 4.56 mg, 6.84 mg, 9.12 mg, or 13.68 mg ropinirole hydrochloride equivalent to ropinirole 2 mg, 4 mg, 6 mg, 8 mg, or 12 mg, respectively. Inactive ingredients consist of carboxymethylcellulose sodium, colloidal silicon dioxide, hydrogenated castor oil, hypromellose, magnesium stearate, povidone, pregelatinized starch, ethylcellulose and one or more of the following: FD&C Blue No. 2 aluminum lake, ferric oxides (black, red, yellow), polyethylene glycol 6000, polyethylene glycol 8000, titanium dioxide, talc.

12 CLINICAL PHARMACOLOGY

12.1 Mechanism of Action

Ropinirole is a non-ergoline dopamine agonist.

The precise mechanism of action of ropinirole as a treatment for Parkinson’s disease is unknown, although it is thought to be related to its ability to stimulate dopamine D2-type receptors within the caudate-putamen in the brain.

12.2 Pharmacodynamics

Clinical experience with dopamine agonists, including ropinirole, suggests an association with impaired ability to regulate blood pressure with resulting orthostatic hypotension, especially during dose escalation. In some subjects in clinical trials, blood pressure changes were associated with the emergence of orthostatic symptoms, bradycardia, and, in one case in a healthy volunteer, transient sinus arrest with syncope [see Warnings and Precautions (5.2, 5.3)].

The mechanism of orthostatic hypotension induced by ropinirole is presumed to be due to a D2-mediated blunting of the noradrenergic response to standing and subsequent decrease in peripheral vascular resistance. Nausea is a common concomitant symptom of orthostatic signs and symptoms.

At oral doses as low as 0.2 mg, ropinirole suppressed serum prolactin concentrations in healthy male volunteers.

Immediate-release ropinirole had no dose-related effect on ECG wave form and rhythm in young, healthy, male volunteers in the range of 0.01 to 2.5 mg.

Immediate-release ropinirole had no dose- or exposure-related effect on mean QTc intervals in healthy male and female volunteers titrated to doses up to 4 mg/day. The effect of ropinirole on QTc intervals at higher exposures achieved either due to drug interactions, hepatic impairment, or at higher doses has not been systematically evaluated.

12.3 Pharmacokinetics

Increase in systemic exposure of ropinirole following oral administration of 2 to 12 mg of ropinirole extended-release tablets was approximately dose-proportional. For ropinirole extended-release tablets, steady-state concentrations of ropinirole are expected to be achieved within 4 days of dosing.

Absorption

In clinical trials with immediate-release ropinirole, over 88% of a radiolabeled dose was recovered in urine, and the absolute bioavailability was 45% to 55%, indicating approximately 50% first-pass effect.

Relative bioavailability of ropinirole extended-release tablets compared with immediate-release tablets was approximately 100%. In a repeat-dose trial in subjects with Parkinson’s disease using ropinirole extended-release tablets 8 mg, the dose-normalized AUC(0-24) and Cmin for ropinirole extended-release tablets and immediate-release ropinirole were similar. Dose-normalized Cmax was, on average, 12% lower for ropinirole extended-release tablets than for the immediate-release formulation and the median time-to-peak concentration was 6 to 10 hours. In a single-dose trial, administration of ropinirole extended-release tablets to healthy volunteers with food (i.e., high-fat meal) increased AUC by approximately 30% and Cmax by approximately 44%, compared with dosing under fasted conditions. In a repeat-dose trial in patients with Parkinson’s disease, food (i.e., high-fat meal) increased AUC by approximately 20% and Cmax by approximately 44%; Tmax was prolonged by 3 hours (median prolongation) compared with dosing under fasted conditions [see Dosage and Administration (2)].

Distribution

Ropinirole is widely distributed throughout the body, with an apparent volume of distribution of 7.5 L/kg. It is up to 40% bound to plasma proteins and has a blood-to-plasma ratio of 1:1.

Metabolism

Ropinirole is extensively metabolized by the liver. The major metabolic pathways are N-despropylation and hydroxylation to form the inactive N-despropyl metabolite and hydroxy metabolites. The N-despropyl metabolite is converted to carbamyl glucuronide, carboxylic acid, and N-despropyl hydroxy metabolites. The hydroxy metabolite of ropinirole is rapidly glucuronidated.

In vitro studies indicate that the major cytochrome P450 enzyme involved in the metabolism of ropinirole is CYP1A2, an enzyme known to be induced by smoking and omeprazole, and inhibited by, for example, fluvoxamine, mexiletine, and the older fluoroquinolones such as ciprofloxacin and norfloxacin.

Elimination

The clearance of ropinirole after oral administration to patients is 47 L/hr and its elimination half-life is approximately 6 hours. Less than 10% of the administered dose is excreted as unchanged drug in urine. N-despropyl ropinirole is the predominant metabolite found in urine (40%), followed by the carboxylic acid metabolite (10%), and the glucuronide of the hydroxy metabolite (10%).

Drug Interactions

Digoxin: Coadministration of immediate-release ropinirole (2 mg three times daily) with digoxin (0.125 to 0.25 mg once daily) did not alter the steady-state pharmacokinetics of digoxin in 10 patients.

Theophylline: Administration of theophylline (300 mg twice daily, a substrate of CYP1A2) did not alter the steady-state pharmacokinetics of immediate-release ropinirole (2 mg three times daily) in 12 patients with Parkinson’s disease. Immediate-release ropinirole (2 mg three times daily) did not alter the pharmacokinetics of theophylline (5 mg/kg IV) in 12 patients with Parkinson’s disease.

Ciprofloxacin: Coadministration of ciprofloxacin (500 mg twice daily), an inhibitor of CYP1A2, with immediate-release ropinirole (2 mg three times daily) increased ropinirole AUC by 84% on average and Cmax by 60% (n = 12 patients).

Estrogens: Population pharmacokinetic analysis revealed that estrogens (mainly ethinylestradiol: intake 0.6 to 3 mg over 4-month to 23-year period) reduced the oral clearance of ropinirole by 36% in 16 patients.

L-dopa: Coadministration of carbidopa + L-dopa (10/100 mg twice daily) with immediate-release ropinirole (2 mg three times daily) had no effect on the steady-state pharmacokinetics of ropinirole (n = 28 patients). Oral administration of immediate-release ropinirole 2 mg three times daily increased mean steady-state Cmax of L-dopa by 20%, but its AUC was unaffected (n = 23 patients).

Commonly Administered Drugs: Population analysis showed that commonly administered drugs, e.g., selegiline, amantadine, tricyclic antidepressants, benzodiazepines, ibuprofen, thiazides, antihistamines, and anticholinergics, did not affect the clearance of ropinirole. An in vitro study indicates that ropinirole is not a substrate for P-gp. Ropinirole and its circulating metabolites do not inhibit or induce P450 enzymes; therefore, ropinirole is unlikely to affect the pharmacokinetics of other drugs by a P450 mechanism.

Specific Populations

Because therapy with ropinirole extended-release tablets is initiated at a low dose and gradually titrated upward according to clinical tolerability to obtain the optimum therapeutic effect, adjustment of the initial dose based on gender, weight, or age is not necessary.

Age: Oral clearance of ropinirole is reduced by 15% in patients.older than 65 years compared with younger patients. Dosage adjustment is not necessary in the elderly (older than 65 years), as the dose of ropinirole is to be individually titrated to clinical response.

Gender: Female and male patients showed similar clearance.

Race: The influence of race on the pharmacokinetics of ropinirole has not been evaluated.

Cigarette Smoking: Smoking is expected to increase the clearance of ropinirole since CYP1A2 is known to be induced by smoking. In a trial in patients with Restless Legs Syndrome, smokers (n =7) had an approximately 30% lower Cmax and a 38% lower AUC than did nonsmokers (n = 11) when those parameters were normalized for dose.

Renal Impairment: Based on population pharmacokinetic analysis, no difference was observed in the pharmacokinetics of ropinirole in subjects with moderate renal impairment (creatinine clearance between 30 to 50 mL/min) compared with an age-matched population with creatinine clearance above 50 mL/min. Therefore, no dosage adjustment is necessary in patients with moderate renal impairment.

A trial of immediate-release ropinirole in subjects with end-stage renal disease on hemodialysis has shown that clearance of ropinirole was reduced by approximately 30%. The recommended maximum dose should be lower in these patients [see Dosage and Administration (2.2)].

The use of ropinirole in subjects with severe renal impairment (creatinine clearance less than 30 mL/min) without regular dialysis has not been studied.

Hepatic Impairment: The pharmacokinetics of ropinirole have not been studied in patients with hepatic impairment.. Because ropinirole is extensively metabolized by the liver, these patients may have higher plasma levels and lower clearance of ropinirole than patients with normal hepatic function.

Other Diseases: Population pharmacokinetic analysis revealed no change in the clearance of ropinirole in patients with concomitant diseases such as hypertension, depression, osteoporosis/arthritis, and insomnia compared with patients with Parkinson’s disease only.

13 NONCLINICAL TOXICOLOGY

13.1 Carcinogenesis, Mutagenesis, Impairment of Fertility

Carcinogenesis

Two-year carcinogenicity studies of ropinirole were conducted in mice at oral doses of 5, 15, and 50 mg/kg/day and rats at oral doses of 1.5, 15, and 50 mg/kg/day.

In rats, there was an increase in testicular Leydig cell adenomas at all doses tested. The lowest dose tested (1.5 mg/kg/day) is less than the MRHD for Parkinson’s disease (24 mg/day) on a mg/m^2 basis. The endocrine mechanisms believed to be involved in the production of these tumors in rats are not considered relevant to humans.

In mice, there was an increase in benign uterine endometrial polyps at a dose of 50 mg/kg/day. The highest dose not associated with this finding (15 mg/kg/day) is three times the MRHD on a mg/m^2 basis.

Mutagenesis

Ropinirole was not mutagenic or clastogenic in in vitro (Ames, chromosomal aberration in human lymphocytes, mouse lymphoma tk) assays, or in the in vivo mouse micronucleus test.

Impairment of Fertility

When administered to female rats prior to and during mating and throughout pregnancy, ropinirole caused disruption of implantation at oral doses of 20 mg/kg/day (8 times the MRHD on a mg/m^2 basis) or greater. This effect in rats is thought to be due to the prolactin-lowering effect of ropinirole. In rat studies using a low oral dose (5 mg/kg) during the prolactin-dependent phase of early pregnancy (gestation days 0 to 8), ropinirole did not affect female fertility at oral doses up to 100 mg/kg/day (40 times the MRHD on a mg/m^2 basis). No effect on male fertility was observed in rats at oral doses up to 125 mg/kg/day (50 times the MRHD on a mg/m^2 basis).

14 CLINICAL STUDIES

The effectiveness of ropinirole was initially established with the immediate-release formulation (ropinirole tablets) for the treatment of early and advanced Parkinson’s disease in three randomized, double-blind, placebo-controlled trials.

The effectiveness of ropinirole extended-release tablets in the treatment of Parkinson’s disease was supported by two randomized, double-blind, multicenter clinical trials and clinical pharmacokinetic considerations. One trial conducted in patients with advanced Parkinson’s disease compared ropinirole extended-release tablets with placebo as adjunctive therapy to L-dopa. A second trial compared ropinirole extended-release tablets with ropinirole tablets in patients with early phase Parkinson’s disease not receiving L-dopa.

In these trials a variety of measures were used to assess the effects of treatment (e.g., Unified Parkinson’s Disease Rating Scale [UPDRS] scores, patient diaries recording time “on” and “off,” tolerability of L-dopa dose reductions). The UPDRS is a multi-item rating scale intended to evaluate mentation (Part I), activities of daily living (Part II), motor performance (Part III), and complications of therapy (Part IV). Part III of the UPDRS contains 14 items designed to assess the severity of the cardinal motor findings in patients with Parkinson’s disease (e.g., tremor, rigidity, bradykinesia, postural instability) scored for different body regions and has a maximum (worst) score of 108.

14.1 Trial in Patients with Advanced Parkinson's Disease (with L-dopa)

The effectiveness of ropinirole extended-release tablets as adjunctive therapy to L-dopa in patients with Parkinson’s disease was established in a randomized, double-blind, placebo-controlled, parallel group, 24-week clinical trial in 393 patients (Hoehn & Yahr criteria Stages II-IV) who were not adequately controlled by L-dopa therapy. Patients were allowed to be on concomitant selegiline, amantadine, anticholinergics, and catechol-O-methyltransferase (COMT) inhibitors provided the doses were stable for at least 4 weeks prior to screening and throughout the trial. The primary efficacy endpoint evaluated was the mean change from baseline in total awake time spent “off”.

Patients in this trial had a mean disease duration of 8.6 years, a mean duration of exposure to L-dopa of 6.5 years, had experienced a minimum of 3 hours awake time “off” with a baseline average of approximately 7 hours awake time “off”, and had a mean baseline UPDRS motor score of approximately 30 points with similar mean data in each treatment group. The mean baseline dose of L-dopa in the group receiving ropinirole extended-release tablets was 824 mg/day and 776 mg/day for the placebo group. Patients initiated treatment at 2 mg/day for 1 week followed by increases of 2 mg/day at weekly intervals to a minimum dose of 6 mg/day. The following week, the total daily dose of ropinirole extended-release tablets could be further increased (based upon therapeutic response and tolerability) to 8 mg/day. Once a daily dose of 8 mg/day was reached, the background L-dopa dosage was reduced. Thereafter, the daily dose could be increased by up to 4 mg/day approximately every 2 weeks until an optimal dose was achieved (based upon therapeutic response and tolerability). The mean dose of ropinirole extended-release tablets at the end of Week 24 was 18.8 mg/day. Dose titrations were based upon the degree of symptom control, planned L-dopa dosage reduction, and/or tolerability. The maximum allowed daily dosage for ropinirole extended-release tablets was 24 mg/day.

The primary efficacy endpoint was mean change from baseline in total awake time spent “off” at Week 24. At baseline the mean total awake time spent “off” was approximately 7 hours in each treatment group. At Week 24, the total awake time spent “off”, on average, had decreased by approximately 2 hours in the group receiving ropinirole extended-release tablets and by approximately half an hour in the placebo group. The adjusted mean difference in total awake time spent “off” between ropinirole extended-release tablets and placebo was -1.7 hours, which was statistically significant (ANCOVA, P<0.0001). Results for this endpoint showing the statistical superiority of ropinirole extended-release tablets over placebo are presented in Table 3.

Table 3. Change from Baseline in Total Awake Time Spent “Off” at Week 24

 | Ropinirole Extended-Release Tablets (n = 201) | Placebo (n = 190)
Mean “off” time at baseline (hours) | 7 | 7
Mean change from baseline in “off” time (hours) | -2.1 | -0.4

The difference between groups in favor of ropinirole extended-release tablets, with regard to a decrease in total “off” hours, was primarily related to an increase in total “on” hours without troublesome dyskinesia. Patients treated with ropinirole extended-release tabletshad a mean reduction in L-dopa dose of 278 mg/day (34%) while patients treated with placebo had a mean reduction of 164 mg/day (21%). In patients who reduced their L-dopa dose, reduction was sustained in 93% of patients treated with ropinirole extended-release tabletsand in 72% of patients treated with placebo (P<0.001).

14.2 Trial in Patients with Early Parkinson's Disease (without L-dopa)

A 36-week multicenter, double-blind, titration/3-period maintenance, cross-over study compared the efficacy of ropinirole extended-release tabletswith the immediate-release formulation of ropinirole tablets(IR) in 161 patients with early phase Parkinson’s disease (Hoehn & Yahr Stages I-III) with limited prior exposure to L-dopa or dopamine agonists. Eligible subjects were randomized (1:1:1:1) to 4 treatment sequences (2 were titrated on ropinirole tabletsIR and 2 on ropinirole extended-release tablets). Titration rate of ropinirole tablets IR was slower than that of the ropinirole extended-release tablets. Patients were titrated, during the 12-week titration period, to their optimal dosage, based upon tolerance and therapeutic response. This was followed by three consecutive 8-week maintenance periods, during which patients were either maintained on the prior formulation or switched to the alternative formulation. All switches were performed overnight by using the approximately equivalent doses of ropinirole. The primary efficacy endpoint was the change of UPDRS motor score within each maintenance period.
Patients in all four groups started out with similar UPDRS motor scores (about 21) at baseline. All 4 groups exhibited similar improvement in UPDRS total motor scores from baseline until the completion of the titration phase, with a change in score of about -9 observed for the groups started on ropinirole tabletsIR and of about -10 for the groups started on ropinirole extended-release tablets. No difference was observed between groups when switches were made between identical formulations or between different formulations. This suggests therapeutic dosage equivalence betweenformulations of ropinirole tabletsIR and ropinirole extended-release tabletsformulations.
The optimal daily dose at the end of the titration period for patients on ropinirole tabletsIR was substantially lower (mean 7 mg) compared with the dose at the end of the titration period for patients on ropinirole extended-release tablets(mean 18 mg). In this trial, the marked difference in the final optimal dosages suggests that the higher doses afforded no additional benefit when compared with the lower doses [see Dosage and Administration (2.2)].

16 HOW SUPPLIED/STORAGE AND HANDLING

Each capsule shaped, film coated tablet contains ropinirole hydrochloride equivalent to the labeled amount of ropinirole as follows:

2 mg: pink tablets debossed with 'L191'

NDC 46708-262-30 bottle of 30 tablets

NDC 46708-262-90 bottle of 90 tablets

NDC 46708-262-31 bottle of 100 tablets
NDC 46708-262-71 bottle of 500 tablets
NDC 46708-262-91 bottle of 1000 tablets

NDC 46708-262-10 carton of 100 (10X10) unit dose tablets

4 mg: light brown tablets debossed with 'L193'

NDC 46708-263-30 bottle of 30 tablets

NDC 46708-263-90 bottle of 90 tablets

NDC 46708-263-31 bottle of 100 tablets
NDC 46708-263-71 bottle of 500 tablets
NDC 46708-263-91 bottle of 1000 tablets

NDC 46708-263-10 carton of 100 (10X10) unit dose tablets

6 mg: white to off white tablets debossed with 'L321'

NDC 46708-264-30 bottle of 30 tablets

NDC 46708-264-90 bottle of 90 tablets

NDC 46708-264-31 bottle of 100 tablets
NDC 46708-264-71 bottle of 500 tablets
NDC 46708-264-91 bottle of 1000 tablets

NDC 46708-264-10 carton of 100 (10X10) unit dose tablets

8 mg: dark brown to red tablets debossed with 'L194'

NDC 46708-265-30 bottle of 30 tablets

NDC 46708-265-90 bottle of 90 tablets

NDC 46708-265-31 bottle of 100 tablets
NDC 46708-265-71 bottle of 500 tablets
NDC 46708-265-91 bottle of 1000 tablets

NDC 46708-265-10 carton of 100 (10X10) unit dose tablets

12 mg: light green tablets debossed with 'L195'

NDC 46708-266-30 bottle of 30 tablets

NDC 46708-266-90 bottle of 90 tablets

NDC 46708-266-31 bottle of 100 tablets
NDC 46708-266-71 bottle of 500 tablets
NDC 46708-266-91 bottle of 1000 tablets

NDC 46708-266-10 carton of 100 (10X10) unit dose tablets

Storage

Store at 20° to 25°C (68° to 77°F). [See USP Controlled Room Temperature.]

Dispense in a tight, light-resistant container as defined in the USP.

17 PATIENT COUNSELING INFORMATION

Advice the patient to read the FDA-approved patient labeling (Patient Information).

Dosing Instructions

- Instruct patients to take ropinirole extended-release tablets only as prescribed. If a dose is missed, advise patients not to double their next dose. Ropinirole extended-release tablets can be taken with or without food. Inform patients to swallow ropinirole extended-release tablets whole and not to chew, crush, or divide the tablets [see Dosage and Administration (2.1)].
- Ropinirole is the active ingredient in both ropinirole extended-release tablets and ropinirole tablets (the immediate-release formulation). Ask your patients if they are taking another medication containing ropinirole.

Hypersensitivity/Allergic Reactions

Advise patients about the potential for developing a hypersensitivity/allergic reaction including manifestations such as urticaria, angioedema, rash, and pruritus when taking any ropinirole product. Inform patients who experience these or similar reactions after starting ropinirole tablets or ropinirole extended-release tablets, to immediately contact their healthcare professional [see Contraindications (4)].

Falling Asleep during Activities of Daily Living and Somnolence

Alert patients to the potential sedating effects caused by ropinirole extended-release tablets, including somnolence and the possibility of falling asleep while engaged in activities of daily living. Because somnolence is a frequent adverse reaction with potentially serious consequences, patients should not drive a car, operate machinery, or engage in other potentially dangerous activities until they have gained sufficient experience with ropinirole extended-release tablets to gauge whether or not it affects their mental and/or motor performance adversely. Advise patients that if increased somnolence or episodes of falling asleep during activities of daily living (e.g., conversations, eating, driving a motor vehicle, etc.) are experienced at any time during treatment, they should not drive or participate in potentially dangerous activities until they have contacted their physician.

Advise patients of possible additive effects when patients are taking other sedating medications, alcohol, or other central nervous system depressants (e.g., benzodiazepines, antipsychotics, antidepressants, etc.) in combination with ropinirole extended-release tablets or when taking a concomitant medication (e.g., ciprofloxacin) that increases plasma levels of ropinirole [see Warnings and Precautions (5.1)].

Syncope and Hypotension/Orthostatic Hypotension

Advise patients that they may experience syncope and may develop hypotension with or without symptoms such as dizziness, nausea, syncope, and sometimes sweating while taking ropinirole extended-release tablets, especially if they are elderly. Hypotension and/or orthostatic symptoms may occur more frequently during initial therapy or with an increase in dose at any time (cases have been seen after weeks of treatment). Postural/orthostatic symptoms may be related to sitting up or standing. Accordingly, caution patients against standing rapidly after sitting or lying down, especially if they have been doing so for prolonged periods and especially at the initiation of treatment with ropinirole extended-release tablets[see Warnings and Precautions (5.2, 5.3)].

Elevation of Blood Pressure and Changes in Heart Rate

Alert patients to the possibility of increases in blood pressure during treatment with ropinirole extended-release tablets. Exacerbation of hypertension may occur. Medication dose adjustment may be necessary if elevation of blood pressure is sustained over multiple evaluations. Alert patients with cardiovascular disease, who may not tolerate marked changes in heart rate, to the possibility that they may experience significant increases or decreases in heart rate during treatment with ropinirole extended-release tablets[see Warnings and Precautions (5.4)].

Hallucinations/Psychotic-like Behavior

Inform patients that they may experience hallucinations (unreal visions, sounds, or sensations) and other psychotic-like behavior can occur while taking ropinirole. The elderly are at greater risk than younger patients with Parkinson’s disease. This risk is greater in patients who are taking ropinirole with L-dopa or taking higher doses of ropinirole, and may also be further increased in patients taking any other drugs that increase dopaminergic tone. Tell patients to report hallucinations or psychotic-like behavior to their healthcare provider promptly should they develop[see Warnings and Precautions (5.5)].

Dyskinesia

Inform patients that ropinirole extended-release tablets may cause and/or exacerbate pre-existing dyskinesias [see Warnings and Precautions (5.6)].

Impulse Control/ Compulsive Behaviors

Advise patients that they may experience impulse control and/or compulsive behaviors while taking one or more of the medications (including ropinirole extended-release tablets) that increase central dopaminergic tone, that are generally used for the treatment of Parkinson’s disease. Advise patients to inform their physician or healthcare provider if they develop new or increased gambling urges, sexual urges, uncontrolled spending, binge or compulsive eating, or other urges while being treated with ropinirole extended-release tablets. Physicians should consider dose reduction or stopping the medication if a patient develops such urges while taking ropinirole extended-release tablets[see Warnings and Precautions (5.7)].

Withdrawal-emergent Hyperpyrexia and Confusion

Advise patients to contact their healthcare provider if they wish to discontinue ropinirole extended-release tablets or decrease the dose of ropinirole extended-release tablets [see Warnings and Precautions (5.8)].

Melanoma

Advise patients with Parkinson’s disease that they have a higher risk of developing melanoma. Advise patients to have their skin examined on a regular basis by a qualified healthcare provider (e.g., dermatologist) when using ropinirole extended-release tablets[see Warnings and Precautions (5.9)].

Nursing Mothers

Because of the possibility that ropinirole may be excreted in breast milk, a decision should be made whether to discontinue nursing or to discontinue the drug, taking into account the importance of the drug to the mother [see Use in Specific Populations (8.3)]. Advise patients that ropinirole extended-release tablets could inhibit lactation because ropinirole inhibits prolactin secretion.

Pregnancy

Because ropinirole has been shown to have adverse effects on embryo-fetal development, including teratogenic effects, in animals, and because experience in humans is limited, advice patients to notify their physician if they become pregnant or intend to become pregnant during therapy [see Use in Specific Populations (8.1)].

Patient Information

Ropinirole Extended-Release Tablets

Important Note: Ropinirole extended-release tablets have not been studied in Restless Legs Syndrome (RLS) and are not approved for the treatment of RLS. However, an immediate-release form of ropinirole is approved for the treatment of moderate to severe primary RLS.

Read this information completely before you start taking ropinirole extended-release tablets. Read the information each time you get more medicine. There may be new information. This leaflet provides a summary about ropinirole extended-release tablets. It does not include everything there is to know about your medicine. This information should not take the place of discussions with your healthcare provider about your medical condition or treatment with ropinirole extended-release tablets.

What is the most important information I should know about ropinirole extended-release tablets?
Ropinirole extended-release tablets can cause serious side effects including:
• Hypersensitivity/allergic reactions. You may experience a hypersensitivity/allergic reaction characterized by hives, rash, itching, and/or swelling of the face, lips, mouth, tongue, or throat, which may cause problems in swallowing or breathing. If you experience any of these reactions, you should not take ropinirole extended-release tablets again until you talk to a healthcare provider and seek their advice.
• Falling asleep during normal activities. You may fall asleep while doing normal activities such as driving a car, doing physical tasks, or using hazardous machinery while taking ropinirole extended-release tablets. You may suddenly fall asleep without being drowsy or without warning. This may result in having accidents. Your chances of falling asleep while doing normal activities while taking ropinirole extended-release tablets are greater if you take other medicines that cause drowsiness. Tell your healthcare provider right away if this happens. Before starting ropinirole extended-release tablets, be sure to tell your healthcare provider if you take any medicines that make you drowsy.
• Fainting. Fainting can happen, and sometimes your heart rate may be decreased. This can happen especially when you start taking ropinirole extended-release tablets or your dose is increased. Tell your healthcare provider if you faint or feel dizzy or light-headed.
• Decrease in blood pressure. Ropinirole extended-release tablets can decrease your blood pressure. Decreases in your blood pressure (hypotension) can happen, especially when you start taking ropinirole extended-release tablets or when your dose is changed. If you faint or feel dizzy, nauseated, or sweaty when you stand up from sitting or lying down (orthostatic hypotension), this may mean that your blood pressure is decreased. When you change position from lying down or sitting to standing up, you should do it carefully and slowly. Call your healthcare provider if you have any of the symptoms of decreased blood pressure listed above.
• Increase in blood pressure. Ropinirole extended-release tablets may increase your blood pressure.
• Changes in heart rate (decrease or increase). Ropinirole extended-release tablets can decrease or increase your heart rate.
• Hallucinations and other psychotic-like behavior. Ropinirole extended-release tablets can cause or worsen psychotic-like behavior including hallucinations (seeing or hearing things that are not real), confusion, excessive suspicion, aggressive behavior, agitation, delusional beliefs (believing things that are not real), and disorganized thinking. The chances of having hallucinations or these other psychotic-like changes are higher in people with Parkinson’s disease who are taking ropinirole extended-release tablets or taking higher doses of these drugs. If you have hallucinations or any of these other psychotic-like changes, talk with your healthcare provider.
•Uncontrolled sudden movements. Ropinirole extended-release tablets may cause uncontrolled sudden movements or make such movements you already have worse or more frequent. Tell your healthcare provider if this happens. The doses of your anti-Parkinson’s medicines may need to be changed.
•Unusual urges. Some patients taking ropinirole extended-release tablets get urges to behave in a way unusual for them. Examples of this are an unusual urge to gamble, increased sexual urges and behaviors, or an uncontrollable urge to shop, spend money, or eat. If you notice or your family notices that you are developing any unusual behaviors, talk to your healthcare provider.
• Increased chance of skin cancer (melanoma). People with Parkinson’s disease may have a higher chance of getting melanoma. It is not known if ropinirole extended-release tablets increase your chances of getting melanoma. You and your healthcare provider should check your skin on a regular basis. Tell your healthcare provider right away if you notice any changes in your skin such as a change in the size, shape, or color of moles on your skin.

What are ropinirole extended-release tablets?
Ropinirole extended-release tablets are long-acting prescription medicine containing ropinirole (taken 1 time a day) that is used only to treat Parkinson’s disease but not to treat Restless Legs Syndrome (RLS).
Having one of these conditions does not mean you have or will develop the other condition.
You should not be taking more than 1 medicine containing ropinirole. Tell your healthcare provider if you are taking any other medicine containing ropinirole.
It is not known if ropinirole extended-release tablets are safe and effective for use in children younger than 18 years of age.

Who should not take ropinirole extended-release tablets?
Do not take ropinirole extended-release tablets if you:
• are allergic to ropinirole or any of the ingredients in ropinirole extended-release tablets. See the end of this page for a complete list of the ingredients in ropinirole extended-release tablets.
Call your healthcare provider and get help right away if you have any of the following symptoms of an allergic reaction. Symptoms of an allergic reaction may include:
• hives
• rash
• swelling of the face, lips, mouth, tongue, or throat
• itching

What should I tell my healthcare provider before taking ropinirole extended-release tablets?
Before you take ropinirole extended-release tablets, tell your healthcare provider if you:
• have daytime sleepiness from a sleep disorder or have unexpected or unpredictable sleepiness or periods of sleep.
• are taking any other prescription or over-the-counter medicines. Some of these medicines may increase your chances of getting side effects while taking ropinirole extended-release tablets.
• start or stop taking other medicines while you are taking ropinirole extended-release tablets. This may increase your chances of getting side effects.
• start or stop smoking while you are taking ropinirole extended-release tablets. Smoking may decrease the treatment effect of ropinirole extended-release tablets.
• feel dizzy, nauseated, sweaty, or faint when you first stand up from sitting or lying down.
• drink alcoholic beverages. This may increase your chances of becoming drowsy or sleepy while taking ropinirole extended-release tablets.
• have high or low blood pressure.
• have or have had heart problems.
• are pregnant or plan to become pregnant. Ropinirole extended-release tablets should only be used during pregnancy if needed.
• are breastfeeding. It is not known if ropinirole extended-release tablets passes into your breast milk. Talk to your healthcare provider to decide whether you will breastfeed or take ropinirole extended-release tablets.
• have any other medical conditions.

How should I take ropinirole extended-release tablets for Parkinson’s disease?
• Take ropinirole extended-release tablets exactly as directed by your healthcare provider.
• Do not suddenly stop taking ropinirole extended-release tablets without talking to your healthcare provider. If you stop this medicine suddenly, you may develop fever, confusion, or severe muscle stiffness.
• Before starting ropinirole extended-release tablets, you should talk to your healthcare provider about what to do if you miss a dose. If you have missed the previous dose and it is time for your next dose, do not double the dose.
• Your healthcare provider will start you on a low dose of ropinirole extended-release tablets. Your healthcare provider will change the dose until you are taking the right amount of medicine to control your symptoms. It may take several weeks before you reach a dose that controls your symptoms.
If you are taking ropinirole extended-release tablets:
• Take ropinirole extended-release tablets 1 time each day for Parkinson’s disease, preferably at or around the same time of day.
• Swallow ropinirole extended-release tablets whole. Do not chew, crush, or split ropinirole extended-release tablets.
• Ropinirole extended-release tablets release drug over a 24-hour period. If you have a condition where medicine passes through your body too quickly, such as diarrhea, the tablet(s) may not dissolve completely and you may see tablet residue in your stool. If this happens, let your healthcare provider know as soon as possible.
• Contact your healthcare provider if you stop taking ropinirole extended-release tablets for any reason. Do not restart without talking with your healthcare provider.
• Your healthcare provider may prescribe ropinirole extended-release tablets alone, or add ropinirole extended-release tablets to medicine that you are already taking for Parkinson’s disease.
• You should not substitute ropinirole extended-release tablets for ropinirole tablets without talking with your healthcare provider.
• You can take ropinirole extended-release tablets with or without food.
What are the possible side effects of ropinirole extended-release tablets?
Ropinirole extended-release tablets can cause serious side effects including:
See “What is the most important information I should know about ropinirole extended-release tablets?”
The most common side effects of ropinirole extended-release tablets include:
• fainting

• sleepiness or drowsiness

• hallucinations (seeing or hearing things that are not real)
• dizziness
• nausea or vomiting
• uncontrolled sudden movements
• leg swelling
• fatigue, tiredness, or weakness
• confusion
• headache
• upset stomach, abdominal pain or discomfort
• increased sweating

Tell your healthcare provider if you have any side effect that bothers you or does not go away.
This is not a complete list of side effects and should not take the place of talking with your healthcare provider. Your healthcare provider or pharmacist can give you a more complete list of possible side effects.

Call your doctor for medical advice about side effects. You may report side effects to FDA at 1-800-FDA-1088.

How should I store ropinirole extended-release tablets?

• Store ropinirole extended-release tablets at room temperature between 20° to 25°C (68° to 77°F).
• Keep ropinirole extended-release tablets in a tightly closed container and out of direct sunlight.

Keep ropinirole extended-release tablets and all medications out of reach of children.

General information about the safe and effective use of ropinirole extended-release tablets:
Medicines are sometimes prescribed for purposes other than those listed in a Patient Information leaflet. Do not take ropinirole extended-release tablets for a condition for which it was not prescribed. Do not give ropinirole extended-release tablets to other people, even if they have the same symptoms you have. It may harm them.
This side of the patient information leaflet summarizes the most important information about ropinirole extended-release tablets for Parkinson’s disease. If you would like more information, talk with your healthcare provider or pharmacist. You can ask your healthcare provider or pharmacist for information about ropinirole extended-release tablets that is written for healthcare professionals.

What are the ingredients in ropinirole extended-release tablets?
Active ingredient: ropinirole (as ropinirole hydrochloride)
Inactive ingredients: carboxymethylcellulose sodium, colloidal silicon dioxide, hydrogenated castor oil, hypromellose, magnesium stearate, povidone, pregelatinized starch, ethylcellulose and one or more of the following: FD&C Blue No. 2 aluminum lake, ferric oxides (black, red, yellow), polyethylene glycol 6000, polyethylene glycol 8000, titanium dioxide, talc.
This Patient Information has been approved by the U.S. Food and Drug Administration.

Manufactured by:
Alembic Pharmaceuticals Limited (Formulation Division),
Village Panelav, P. O. Tajpura, Near Baska,
Taluka-Halol, Panchmahal, Gujarat, India.
Revised: 01/2016

PACKAGE LABEL.PRINCIPAL DISPLAY PANEL - 2mg

rOPINIRole Extended-Release Tablets 2 mg* (30 Tablets in 1 Bottle)
*Each extended-release tablet contains 2.28 mg ropinirole hydrochloride equivalent to 2 mg ropinirole
46708-262-30

PACKAGE LABEL.PRINCIPAL DISPLAY PANEL - 4mg

rOPINIRole Extended-Release Tablets 4 mg* (30 Tablets in 1 Bottle)
*Each extended-release tablet contains 4.56 mg ropinirole hydrochloride equivalent to 4 mg ropinirole
46708-263-30

PACKAGE LABEL.PRINCIPAL DISPLAY PANEL - 6mg

rOPINIRole Extended-Release Tablets 6 mg* (30 Tablets in 1 Bottle)
*Each extended-release tablet contains 6.84 mg ropinirole hydrochloride equivalent to 6 mg ropinirole
46708-264-30

PACKAGE LABEL.PRINCIPAL DISPLAY PANEL - 8mg

rOPINIRole Extended-Release Tablets 8 mg* (30 Tablets in 1 Bottle)
*Each extended-release tablet contains 9.12 mg ropinirole hydrochloride equivalent to 8 mg ropinirole
46708-265-30

PACKAGE LABEL.PRINCIPAL DISPLAY PANEL - 12mg

rOPINIRole Extended-Release Tablets 12 mg* (30 Tablets in 1 Bottle)
*Each extended-release tablet contains 13.68 mg ropinirole hydrochloride equivalent to 12 mg ropinirole
46708-266-30